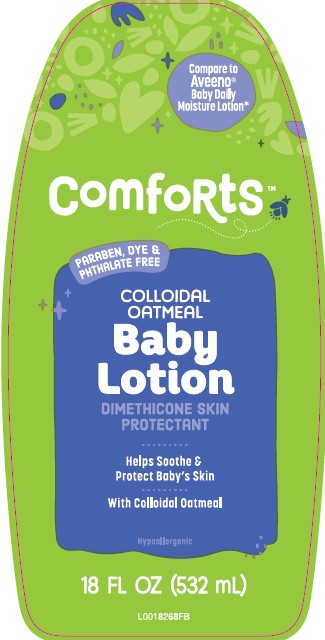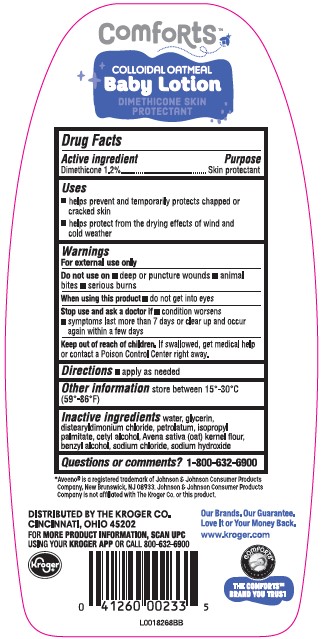 DRUG LABEL: Daily Baby
NDC: 30142-496 | Form: LOTION
Manufacturer: The Kroger Co.
Category: otc | Type: HUMAN OTC DRUG LABEL
Date: 20260227

ACTIVE INGREDIENTS: DIMETHICONE 12 mg/1 mL
INACTIVE INGREDIENTS: WATER; GLYCERIN; DISTEARYLDIMONIUM CHLORIDE; PETROLATUM; ISOPROPYL PALMITATE; CETYL ALCOHOL; OATMEAL; BENZYL ALCOHOL; SODIUM CHLORIDE; SODIUM HYDROXIDE

Kroger 496.000/496AA
Daily Baby Lotion with Colloidal Oatmeal

Claims

Comforts™

COLLOIDAL OATMEAL

Baby Lotion

DIMETHICONE SKIN PROTECTANT

Active ingredient

Dimethcone 1.2%

Purpose

Skin protectant

Uses

- helps prevent and temporarily protects chapped or cracked skin
- helps protect from the drying effects of wind and cold weather

Warnings

For external use only

Do not use on

- deep or puncture wounds
- animal bites
- serious burns

When using this product

do not get into eyes

Stop use and ask a doctor if

- condition worsens
- symptoms last more than 7 days or clear up and occur again within in a few days

Keep out of reach of children.

If swallowed, get medical help or contact a Poison Control Center right away.

Directions

- apply as needed

Other information

store between 15°-30°C (59°-86°F)

Inactive ingredients

water, glycerin, distearyldimonium chloride, petrolatum, isopropyl palmitate, cetyl alcohol, Avea sativa (oat) kernel flour, benzyl alcohol, sodium chloride, sodium hydroxide

Questions or Comments?

1-800-632-6900

Disclaimer

*Aveenois registered trademark of Johnson & Johnson Consumer Products Company, New Brunswick, NJ 08933. Johnson & Johnson Consumer Products Company is not affiliated with The Kroger Co. or this product.

ADVERSE REACTION

Distributed by the Kroger CO.

Cincinnati, Ohio 45202

For more product information, scan UPC using your Kroger APP or call 800-632-6900

Kroger

Our Brands. Our Guarantee.

Love it or your money back.

www.kroger.com

The Comforts™ Brand you trust

principal display panel

Compare to Aveeno®Baby Daily Moisture Lotion*

Comforts™

Paraben, Dye & Phthalate Free

Colloidal Oatmeal

Baby Lotion

Dimethicone Skin Protectant

Helps soothe & protect baby's skin

With Colloidal Oatmeal

Hypoallergenic

18 FL OZ (532 mL)